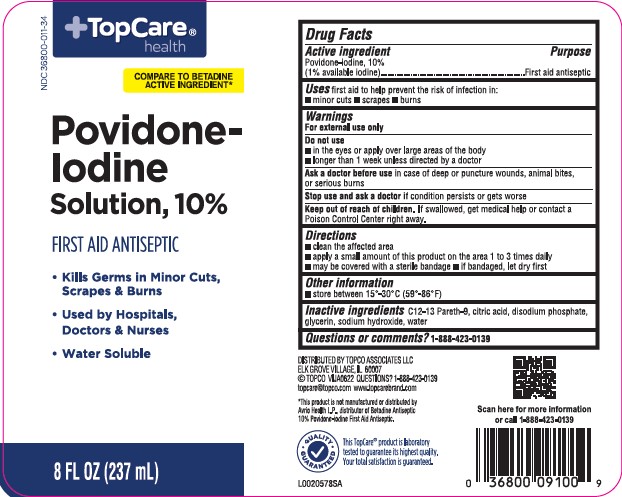 DRUG LABEL: First Aid Antiseptic
NDC: 36800-011 | Form: SOLUTION
Manufacturer: Topco Associates LLC
Category: otc | Type: HUMAN OTC DRUG LABEL
Date: 20260213

ACTIVE INGREDIENTS: POVIDONE-IODINE 10 mg/1 mL
INACTIVE INGREDIENTS: C12-13 PARETH-9; CITRIC ACID MONOHYDRATE; SODIUM PHOSPHATE, DIBASIC, ANHYDROUS; GLYCERIN; SODIUM HYDROXIDE; WATER

Top Care 050.002/050AE
Povidone Iodine Solution

Active ingredient

Povidone-iodine, 10% (1% available iodine)

Purpose

First aid antiseptic

Uses

first aid to help prevent the risk of infection in:

- minor cuts
- scrapes
- burns

Warnings

For external use only

Do not use

- in the eyes or apply over large areas of the body
- longer than 1 week unless directed by a doctor

Ask a doctor before use

in case of deep or puncture counds, animal bites, or serious burns

stop use and ask a doctor if

condition persists or gets worse

keep out of reach of children.

If swallowed, get medical help or contact a Poison Control Center right away.

Directions

- clean the affected area
- apply a small amount of this product on the area 1 to 3 times daily
- may be covered with a sterile bandage.
- if bandaged, let dry first.

Other information

- store between 15º-30ºC (59º-86ºF)

inactive ingredents

C12-13 Pareth-9, citric acid, disodium phosphate, glycerin, sodium hydroxide, water

ADVERSE REACTION

DISTRIBUTED BY TOPCO ASSOCIATES LLC

ELK GROVE VILLAGE, IL 60007

©TOPCO VIJA0622 QUESTIONS? 1-888-423-0139

topcare@topco.com www.topcarebrand.com

*This product is not manufactured or distributed by Avrio Health L.P., distributor of Betadine Antiseptic 10% Povidone-Iodine First Aid Antiseptic.

Quality Guaranteed

This TopCareproduct is laboratory tested to guarantee its highest quality.

Your total satisfaction is guaranteed.

Scan here for more information or call 1-888-423-0139

principal display panel

NDC 36800-011-34

TopCare®health

Compare to Betadine Active Ingredient*

Povidone-Iodine Solution, 10%

FIRST AID ANTISEPTIC

- Kills germs in minor cuts, scrapes, and burns
- Used by Hospitals, Doctors & Nurses
- Water Soluble

8 FL OZ (237 mL)